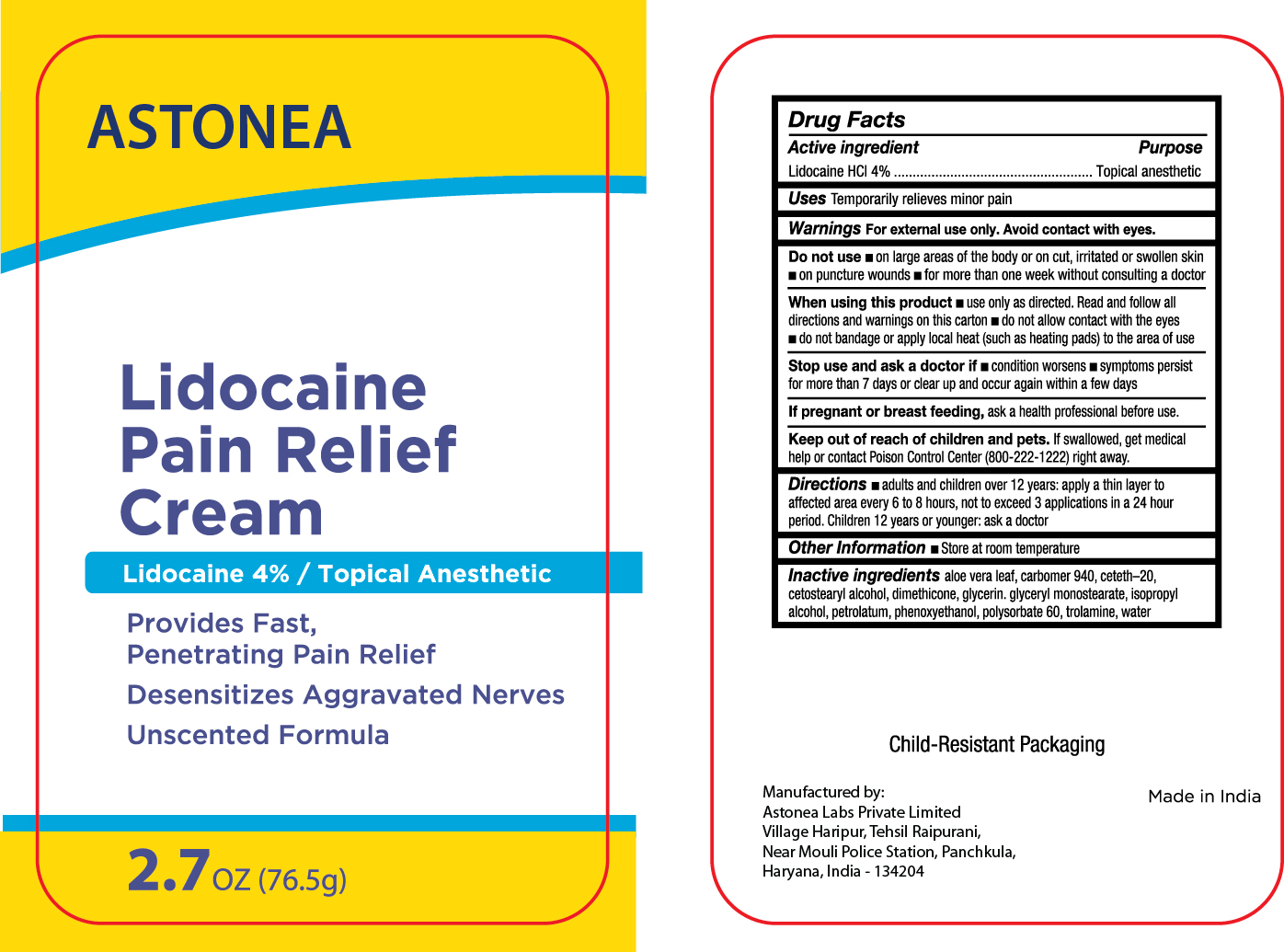 DRUG LABEL: Lidocaine Pain Relief
NDC: 77338-009 | Form: CREAM
Manufacturer: ASTONEA LABS PRIVATE LIMITED
Category: otc | Type: HUMAN OTC DRUG LABEL
Date: 20240312

ACTIVE INGREDIENTS: LIDOCAINE HYDROCHLORIDE 40 mg/1 g
INACTIVE INGREDIENTS: ISOPROPYL ALCOHOL; POLYSORBATE 60; TROLAMINE; DIMETHICONE; ALOE VERA LEAF; CETOSTEARYL ALCOHOL; CETETH-20 PHOSPHATE; GLYCERIN; PHENOXYETHANOL; WATER; CARBOMER 940

ASTONEA LIDOCAINE 4 % CREAM

Active ingredients

Lidocaine HCl 4%

Purpose

Lidocaine HCl - Topical anesthetic

Uses

temporarily relieves minor pain

Warnings

For external use only

Do not use

- on large areas of the body or on cut, irritated or swollen skin
- on puncture wounds
- for more than one week without consulting a doctor

When using this product

- use only as directed
- do not get into eyes
- do not bandage tightly or apply external heat (such as a heating pad) to the area of use

Stop use and ask a doctor if

- condition worsens
- symptoms persist for more than 7 days or clear up and occur again within a few days
- redness, rash, or irritation occurs

If pregnant or breast-feeding,

ask a health professional before use.

Keep out of reach of children.

If swallowed, get medical help or contact Poison Control Center (800-222-1222) right away.

Directions

- adults and children 12 years and over: apply a thin layer to affected area every 6 to 8 hours, not to exceed 3 applications in a 24 hour period
- children under 12 years: ask a doctor

Inactive ingredients

aloe vera leaf, carbomer 940, ceteth-20, cetostearyl alcohol, dimethicone, glycerin. glyceryl monostearate, isopropyl alcohol, petrolatum, phenoxyethanol, polysorbate 60, trolamine, water